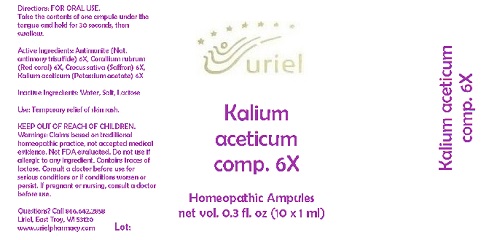 DRUG LABEL: Kalium aceticum comp. 6
NDC: 48951-6006 | Form: LIQUID
Manufacturer: Uriel Pharmacy Inc.
Category: homeopathic | Type: HUMAN OTC DRUG LABEL
Date: 20180426

ACTIVE INGREDIENTS: ANTIMONY TRISULFIDE 6 [hp_X]/1 mL; CORALLIUM RUBRUM EXOSKELETON 6 [hp_X]/1 mL; SAFFRON 6 [hp_X]/1 mL; POTASSIUM ACETATE 6 [hp_X]/1 mL
INACTIVE INGREDIENTS: WATER; SODIUM CHLORIDE; LACTOSE

Kalium aceticum comp. 6

INDICATIONS AND USAGE

Directions: FOR ORAL USE.

DOSAGE AND ADMINISTRATION

Take the contents of one ampule under the tongue and hold for 30 seconds, then swallow.

ACTIVE INGREDIENT

Active Ingredients: Antimonite (Nat. antimony trisulfide) 6X, Corallium rubrum (Red coral) 6X, Crocus sativa (Saffron) 6X, Kalium aceticum (Potassium acetate) 6X

Inactive Ingredients: Water, Salt, Lactose

PURPOSE

Use: Temporary relief of skin rash.

KEEP OUT OF REACH OF CHILDREN.

WARNINGS

Warnings: Claims based on traditional homeopathic practice, not accepted medical evidence. Not FDA evaluated. Do not use if allergic to any ingredient. Contains traces of lactose. Consult a doctor before use for serious conditions or if conditions worsen or persist. If pregnant or nursing, consult a doctor before use.

QUESTIONS

Questions? Call 866.642.2858 Uriel, East Troy, WI 53120 www.urielpharmacy.com